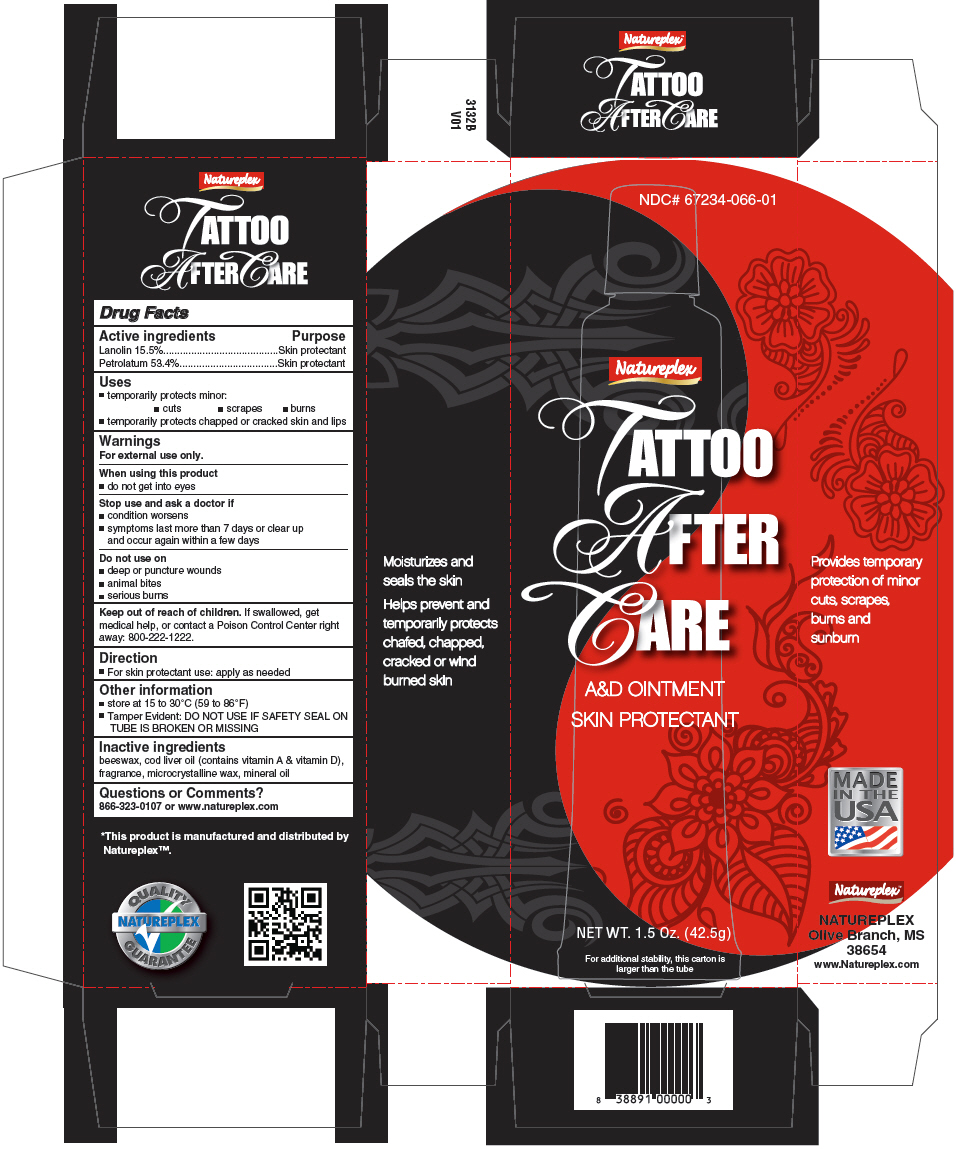 DRUG LABEL: Tattoo After Care 
NDC: 67234-066 | Form: OINTMENT
Manufacturer: Natureplex LLC
Category: otc | Type: HUMAN OTC DRUG LABEL
Date: 20180406

ACTIVE INGREDIENTS: Lanolin 0.15 mg/1 g; Petrolatum 0.53 mg/1 g
INACTIVE INGREDIENTS: WHITE WAX; COD LIVER OIL; MINERAL OIL; MICROCRYSTALLINE WAX

Tattoo After Care
A&D Ointment

Drug Facts

ACTIVE INGREDIENT

Active ingredients | Purpose
Lanolin 15.5% | Skin protectant
Petrolatum 53.4% | Skin protectant

Uses

- temporarily protects minor:
  - cuts
  - scrapes
  - burns
- temporarily protects chapped or cracked skin and lips

Warnings

For external use only.

When using this product

- do not get into eyes

Stop use and ask a doctor if

- condition worsens
- symptoms last more than 7 days or clear up and occur again within a few days

Do not use on

- deep or puncture wounds
- animal bites
- serious burns

Keep out of reach of children. If swallowed, get medical help, or contact a Poison Control Center right away: 800-222-1222.

Direction

- For skin protectant use: apply as needed

Other information

- store at 15 to 30°C (59 to 86°F)
- Tamper Evident: DO NOT USE IF SAFETY SEAL ON TUBE IS BROKEN OR MISSING

Inactive ingredients

beeswax, cod liver oil (contains vitamin A & vitamin D), fragrance, microcrystalline wax, mineral oil

Questions or Comments?

866-323-0107 or www.natureplex.com

*This product is manufactured and distributed by Natureplex™.

PRINCIPAL DISPLAY PANEL - 42.5 g Tube Carton

NDC# 67234-066-01

Natureplex

TATTOO
AFTER
CARE

A&D OINTMENT
SKIN PROTECTANT

NET WT. 1.5 Oz. (42.5g)

For additional stability, this carton is
larger than the tube